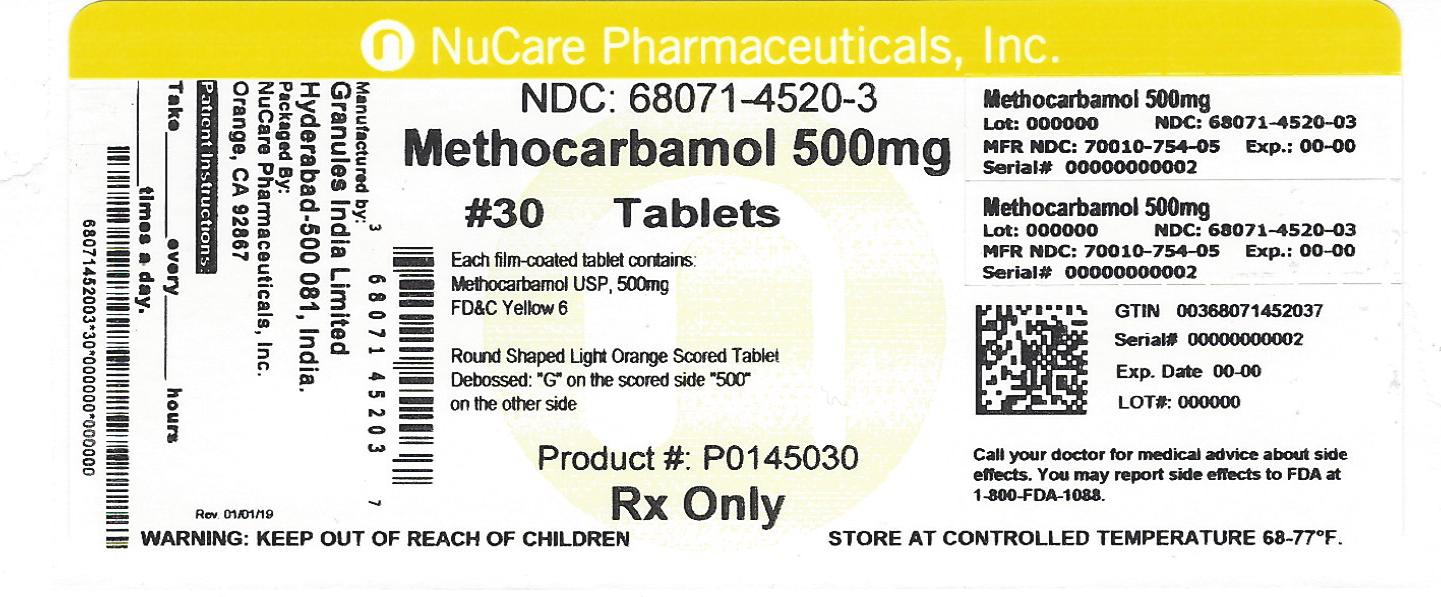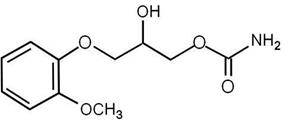 DRUG LABEL: Methocarbamol
NDC: 68071-4520 | Form: TABLET, COATED
Manufacturer: NuCare Pharmaceuticals,Inc.
Category: prescription | Type: HUMAN PRESCRIPTION DRUG LABEL
Date: 20260130

ACTIVE INGREDIENTS: METHOCARBAMOL 500 mg/1 1
INACTIVE INGREDIENTS: POLYSORBATE 80; PROPYLENE GLYCOL; TITANIUM DIOXIDE; SILICON DIOXIDE; STARCH, CORN; POVIDONE; SODIUM LAURYL SULFATE; SODIUM STARCH GLYCOLATE TYPE A POTATO; STEARIC ACID; FD&C YELLOW NO. 6; HYDROXYPROPYL CELLULOSE; HYPROMELLOSE 2910 (6 MPA.S)

Methocarbamol Tablets
Rx Only

DESCRIPTION

Methocarbamol tablet, USP, a carbamate derivative of guaifenesin, is a central nervous system (CNS) depressant with sedative and musculoskeletal relaxant properties.

The chemical name of methocarbamol is 1,2-Propanediol,3-(2-methoxyphenoxy)-,1-Carbamate,(±)-.(or) (±)-3-(o-Methoxyphenoxy)-1,2-Propanediol 1-carbamate and has the empirical formula C11H15NO5. Its molecular weight is 241.24g/mol. The structural formula is shown below.

Methocarbamol is a white powder, sparingly soluble in water and in chloroform, soluble in alcohol (only with heating), insoluble in benzene and in n-hexane.

Methocarbamol tablets, USP are available as 500 mg and 750 mg tablets for oral administration.

Methocarbamol tablets, USP 500 mg are light orange colored, round shaped film coated tablets debossed with "G" above the score line on one side and "500" on other side.

Methocarbamol tablets, USP 750 mg are light orange colored, caplet shaped film coated tablets debossed with "G" on one side and "750" on other side.

Methocarbamol tablets, USP 500 mg and 750 mg contain the following inactive ingredients: colloidal silicon dioxide, maize starch, povidone, sodium lauryl sulfate, sodium starch glycolate, and stearic acid.

The tabets are coated with Aquarius Prime which contains FD&C yellow 6, hydroxypropylcellulose, hypromellose, polysorbate 80, propylene glycol, and titanium dioxide

CLINICAL PHARMACOLOGY

The mechanism of action of methocarbamol in humans has not been established, but may be due to general central nervous system (CNS) depression. It has no direct action on the contractile mechanism of striated muscle, the motor end plate or the nerve fiber.

Pharmacokinetics

In healthy volunteers, the plasma clearance of methocarbamol ranges between 0.20 and 0.80 L/h/kg, the mean plasma elimination half-life ranges between 1 and 2 hours, and the plasma protein binding ranges between 46% and 50%.
Methocarbamol is metabolized via dealkylation and hydroxylation. Conjugation of methocarbamol also is likely. Essentially all methocarbamol metabolites are eliminated in the urine. Small amounts of unchanged methocarbamol also are excreted in the urine.
Special Populations
Elderly
The mean (± SD) elimination half-life of methocarbamol in elderly healthy volunteers (mean (± SD) age, 69 (± 4) years) was slightly prolonged compared to a younger (mean (± SD) age, 53.3 (± 8.8) years), healthy population (1.5 (± 0.4) hours versus 1.1 (± 0.27) hours, respectively). The fraction of bound methocarbamol was slightly decreased in the elderly versus younger volunteers (41 to 43% versus 46 to 50%, respectively).

Renally impaired
The clearance of methocarbamol in 8 renally-impaired patients on maintenance hemodialysis was reduced about 40% compared to 17 normal subjects, although the mean (± SD) elimination half-life in these two groups was similar: 1.2 (± 0.6) versus 1.1 (±0.3) hours, respectively.

Hepatically impaired
In 8 patients with cirrhosis secondary to alcohol abuse, the mean total clearance of methocarbamol was reduced approximately 70% compared to that obtained in 8 age- and weight-matched normal subjects. The mean (± SD) elimination half-life in the cirrhotic patients and the normal subjects was 3.38 (± 1.62) hours and 1.11 (± 0.27) hours, respectively. The percent of methocarbamol bound to plasma proteins was decreased to approximately 40 to 45% compared to 46 to 50% in the normal subjects.

INDICATIONS & USAGE

Methocarbamol tablets, USP are indicated as an adjunct to rest, physical therapy, and other measures for the relief of discomfort associated with acute, painful musculoskeletal conditions. The mode of action of methocarbamol has not been clearly identified, but may be related to its sedative properties. Methocarbamol does not directly relax tense skeletal muscles in man.

CONTRAINDICATIONS

Methocarbamol tablets are contraindicated in patients hypersensitive to methocarbamol or to any of the tablet components.

WARNINGS

Since methocarbamol may possess a general CNS depressant effect, patients receiving Methocarbamol tablets should be cautioned about combined effects with alcohol and other CNS depressants.

Safe use of Methocarbamol tablets has not been established with regard to possible adverse effects upon fetal development. There have been reports of fetal and congenital abnormalities following in utero exposure to methocarbamol. Therefore, Methocarbamol tablets should not be used in women who are or may become pregnant and particularly during early pregnancy unless in the judgment of the physician the potential benefits outweigh the possible hazards (see PRECAUTIONS, Pregnancy).

Use in Activities Requiring Mental Alertness

Methocarbamol may impair mental and/or physical abilities required for performance of hazardous tasks, such as operating machinery or driving a motor vehicle. Patients should be cautioned about operating machinery, including automobiles, until they are reasonably certain that methocarbamol therapy does not adversely affect their ability to engage in such activities.

PRECAUTIONS

INFORMATION FOR PATIENTS

Patients should be cautioned that methocarbamol may cause drowsiness or dizziness, which may impair their ability to operate motor vehicles or machinery.

Because methocarbamol may possess a general CNS-depressant effect, patients should be cautioned about combined effects with alcohol and other CNS depressants.

DRUG INTERACTIONS

See WARNINGS and PRECAUTIONSfor interaction with CNS drugs and alcohol.

Methocarbamol may inhibit the effect of pyridostigmine bromide. Therefore, methocarbamol should be used with caution in patients with myasthenia gravis receiving anticholinesterase agents.

DRUG & OR LABORATORY TEST INTERACTIONS

Methocarbamol may cause color interference in certain screening tests for 5-hydroxyindoleacetic acid (5-HIAA) using nitrosonaphthol reagent and in screening tests for urinary vanillylmandelic acid (VMA) using the Gitlow method.

CARCINOGENESIS & MUTAGENESIS & IMPAIRMENT OF FERTILITY

Long-term studies to evaluate the carcinogenic potential of methocarbamol have not been performed. No studies have been conducted to assess the effect of methocarbamol on mutagenesis or its potential to impair fertility.

PREGNANCY

Teratogenic Effects
Pregnancy Category C
Animal reproduction studies have not been conducted with methocarbamol. It is also not known whether methocarbamol can cause fetal harm when administered to a pregnant woman or can affect reproduction capacity. Methocarbamol tablets should be given to a pregnant woman only if clearly needed.

Safe use of methocarbamol tablet has not been established with regard to possible adverse effects upon fetal development. There have been reports of fetal and congenital abnormalities following in utero exposure to methocarbamol. Therefore, Methocarbamol tablets should not be used in women who are or may become pregnant and particularly during early pregnancy unless in the judgment of the physician the potential benefits outweigh the possible hazards (see WARNINGS).

NURSING MOTHERS

Methocarbamol and/or its metabolites are excreted in the milk of dogs; however, it is not known whether methocarbamol or its metabolites are excreted in human milk. Because many drugs are excreted in human milk, caution should be exercised when methocarbamol tablets are administered to a nursing woman.

PEDIATRIC USE

Safety and effectiveness of methocarbamol tablets in pediatric patients below the age of 16 have not been established.

ADVERSE REACTIONS

Adverse reactions reported coincident with the administration of methocarbamol include:

Body as a whole: Anaphylactic reaction, angioneurotic edema, fever, headache

Cardiovascular system: Bradycardia, flushing, hypotension, syncope, thrombophlebitis

Digestive system: Dyspepsia, jaundice (including cholestatic jaundice), nausea and vomiting

Hemic and lymphatic system: Leukopenia

Immune system: Hypersensitivity reactions

Nervous system: Amnesia, confusion, diplopia, dizziness or lightheadedness, drowsiness, insomnia, mild muscular incoordination, nystagmus, sedation, seizures(including grand mal), vertigo

Skin and special senses: Blurred vision, conjunctivitis, nasal congestion, metallic taste, pruritus, rash, Urticaria

To report SUSPECTED ADVERSE REACTIONS, contact Granules USA, Inc. at 1-877-770-3183 or FDA at 1-800-FDA-1088 or www.fda.gov/medwatch

OVERDOSAGE

Limited information is available on the acute toxicity of methocarbamol. Overdose of methocarbamol is frequently in conjunction with alcohol or other CNS depressants and includes the following symptoms: nausea, drowsiness, blurred vision, hypotension, seizures, and coma.

In post-marketing experience, deaths have been reported with an overdose of methocarbamol alone or in the presence of other CNS depressants, alcohol or psychotropic drugs.

Treatment

Management of overdose includes symptomatic and supportive treatment. Supportive measures include maintenance of an adequate airway, monitoring urinary output and vital signs, and administration of intravenous fluids if necessary. The usefulness of hemodialysis in managing overdose is unknown.

DOSAGE & ADMINISTRATION

Methocarbamol Tablets, USP 500 mg – Adults:
Initial dosage: 3 tablets 4 times daily
Maintenance dosage: 2 tablets 4 times daily
Methocarbamol Tablets, USP 750 mg – Adults:
Initial dosage: 2 tablets 4 times daily
Maintenance dosage: 1 tablet every 4 hours or 2 tablets three times daily

Six grams a day are recommended for the first 48 to 72 hours of treatment. (For severe conditions 8 grams a day may be administered). Thereafter, the dosage can usually be reduced to approximately 4 grams a day.

HOW SUPPLIED

Methocarbamol tablets, USP 500 mg are light orange colored, roundshaped film coated tablets debossed with G above the score line onone side and 500 on other side.

They are supplied as follows

NDC 68071-4520-2 BOTTLES OF 20

NDC 68071-4520-3 BOTTLES OF 30

NDC 68071-4520-6 BOTTLES OF 60

NDC 68071-4520-9 BOTTLES OF 90

Store between 20ºC and 25ºC (68ºF and 77º F)

[see USP Controlled Room Temperature].

Dispense in tight container.

Manufactured for:

Granules USA, Inc.

Parsippany, NJ 07054

Toll-free: 1-877-770-3183

Manufactured by:

Granules India Limited

Hyderabad-500 081

Made in India

Issued: January 2017